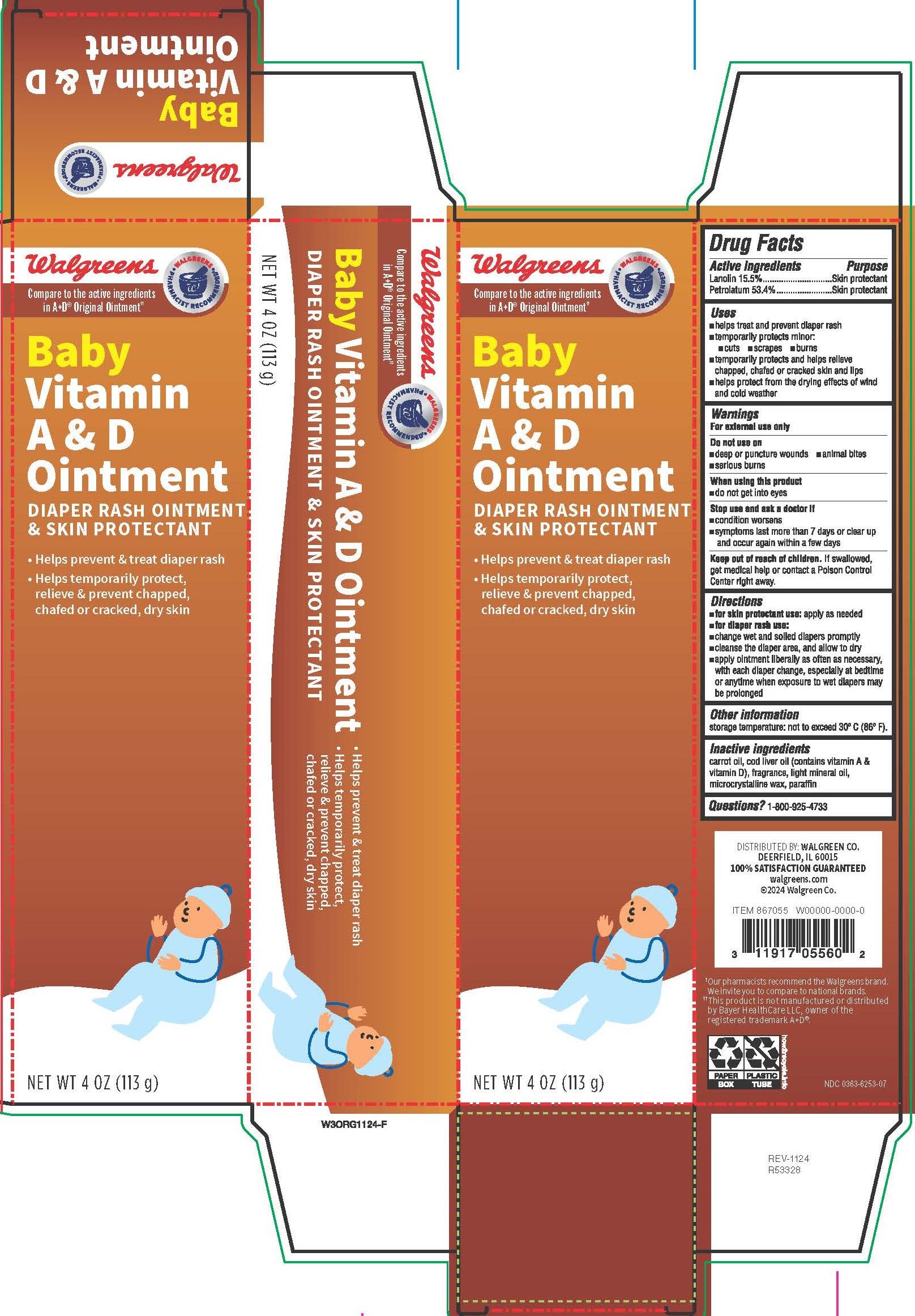 DRUG LABEL: Baby Vitamin A and D
NDC: 0363-6253 | Form: OINTMENT
Manufacturer: Walgreen Company
Category: otc | Type: HUMAN OTC DRUG LABEL
Date: 20251031

ACTIVE INGREDIENTS: LANOLIN 15.5 g/100 g; PETROLATUM 53.4 g/100 g
INACTIVE INGREDIENTS: PARAFFIN; COD LIVER OIL; CARROT SEED OIL; LIGHT MINERAL OIL; MICROCRYSTALLINE WAX

6253 Diaper Rash-Walgreen

Drug Facts

Active ingredients

Lanolin 15.5%

Petrolatum 53.4%

Purpose

Skin protectant

Skin protectant

Uses

- helps treat and prevent diaper rash
- temporarily protects minor:
- cuts
- scrapes
- burns
- temporarily protects and helps relieve chapped, chafed or cracked skin and lips
- helps protect from the drying effects of wind and cold weather

Warnings

For external use only

Do not use on

- deep or puncture wounds
- animal bites
- serious burns

When using this product

- do not get into eyes

Stop use and ask a doctor if

- condition worsens
- symptoms last more than 7 days or clear up and occur again within a few days

Keep out of reach of children.

OVERDOSAGE

If swallowed, get medical help or contact a Poison Control Center right away.

Directions

- for skin protectant use: apply as needed
- for diaper rash use:
- change wet and soiled diapers promptly
- cleanse the diaper area, and allow to dry
- apply ointment liberally as often as necessary, with each diaper change, especially at bedtime or anytime when exposure to wet diapers may be prolonged

Other information

storage temperature: not to exceed 30° C (86° F).

Inactive ingredients

carrot oil, cod liver oil (contains vitamin A & vitamin D), fragrance, light mineral oil, microcrystalline wax, paraffin

Questions?

1-800-925-4733

DISTRIBUTED BY: WALGREEN CO.

DEERFIELD, IL 60015

100% SATISFACTION GUARANTEED

walgreens.com

©2024 Walgreen Co.

†Our pharmacists recommend the Walgreens brand. We invite you to compare to national brands.
††This product is not manufactured or distributed by Bayer HealthCare LLC, owner of the registered trademark A+D®.

NDC 0363-6253-07

PACKAGE LABEL

Walgreens

Walgreens Pharmacist Recommended†

Compare to the active ingredients in A+D® Original Ointment††

Baby Vitamin A & D Ointment

DIAPER RASH OINTMENT & SKIN PROTECTANT

- Helps prevent & treat diaper rash
- Helps temporarily protect, relieve & prevent chapped, chafed or cracked, dry skin

NET WT 4 OZ (113 g)